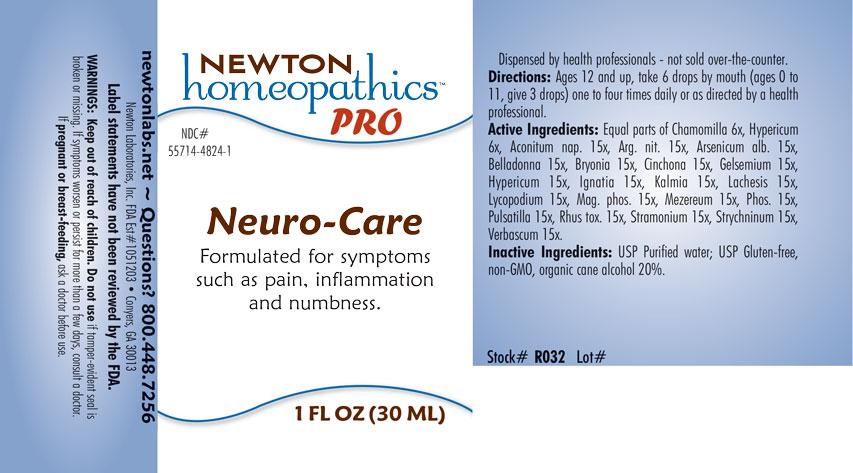 DRUG LABEL: Neuro-Care
NDC: 55714-4824 | Form: LIQUID
Manufacturer: Newton Laboratories, Inc.
Category: homeopathic | Type: HUMAN OTC DRUG LABEL
Date: 20201204

ACTIVE INGREDIENTS: VERBASCUM THAPSUS 15 [hp_X]/1 mL; MATRICARIA CHAMOMILLA 6 [hp_X]/1 mL; STRYCHNINE 15 [hp_X]/1 mL; SILVER NITRITE 15 [hp_X]/1 mL; ARSENIC TRIOXIDE 15 [hp_X]/1 mL; ATROPA BELLADONNA 15 [hp_X]/1 mL; BRYONIA ALBA ROOT 15 [hp_X]/1 mL; CINCHONA OFFICINALIS BARK 15 [hp_X]/1 mL; GELSEMIUM SEMPERVIRENS ROOT 15 [hp_X]/1 mL; HYPERICUM PERFORATUM 15 [hp_X]/1 mL; STRYCHNOS IGNATII SEED 15 [hp_X]/1 mL; KALMIA LATIFOLIA LEAF 15 [hp_X]/1 mL; LACHESIS MUTA VENOM 15 [hp_X]/1 mL; LYCOPODIUM CLAVATUM SPORE 15 [hp_X]/1 mL; MAGNESIUM PHOSPHATE, DIBASIC TRIHYDRATE 15 [hp_X]/1 mL; DAPHNE MEZEREUM BARK 15 [hp_X]/1 mL; PHOSPHORUS 15 [hp_X]/1 mL; ANEMONE PULSATILLA 15 [hp_X]/1 mL; TOXICODENDRON PUBESCENS LEAF 15 [hp_X]/1 mL; DATURA STRAMONIUM 15 [hp_X]/1 mL; ACONITUM NAPELLUS 15 [hp_X]/1 mL
INACTIVE INGREDIENTS: WATER; ALCOHOL

Neuro 4824L

INDICATIONS & USAGE SECTION

Formulated for symptoms such as pain, inflammation and numbness.

DOSAGE & ADMINISTRATION SECTION

Directions: Ages 12 and up, take 6 drops by mouth (ages 0 to 11, give 3 drops) one to four times daily or as directed by a health professional.

OTC - ACTIVE INGREDIENT SECTION

Equal parts of Chamomilla 6x, Hypericum perforatum 6x, Aconitum napellus 15x, Argentum nitricum 15x, Arsenicum album 15x, Belladonna 15x, Bryonia 15x, Cinchona officinalis 15x, Gelsemium sempervirens 15x, Hypericum perforatum 15x, Ignatia amara 15x, Kalmia latifolia 15x, Lachesis mutus 15x, Lycopodium clavatum 15x, Magnesia phosphorica 15x, Mezereum 15x, Phosphorus 15x, Pulsatilla 15x, Rhus toxicodendron 15x, Stramonium 15x, Strychninum 15x, Verbascum thapsus 15x.

OTC - PURPOSE SECTION

Formulated for symptoms such as pain, inflammation and numbness.

INACTIVE INGREDIENT SECTION

Inactive Ingredients: USP Purified Water; USP Gluten-free, non-GMO, organic cane alcohol 20%.

QUESTIONS SECTION

newtonlabs.net - Questions? 800.448.7256

Newton Laboratories, Inc. FDA Est # 1051203 Conyers, GA 30013

WARNINGS SECTION

WARNINGS: Keep out of reach of children. Do not use if tamper-evident seal is broken or missing. If symptoms worsen or persist for more than a few days, consult a doctor. If pregnant or breast-feeding, ask a doctor before use.

OTC - PREGNANCY OR BREAST FEEDING SECTION

If pregnant or breast-feeding, ask a doctor before use.

OTC - KEEP OUT OF REACH OF CHILDREN SECTION

Keep out of reach of children.